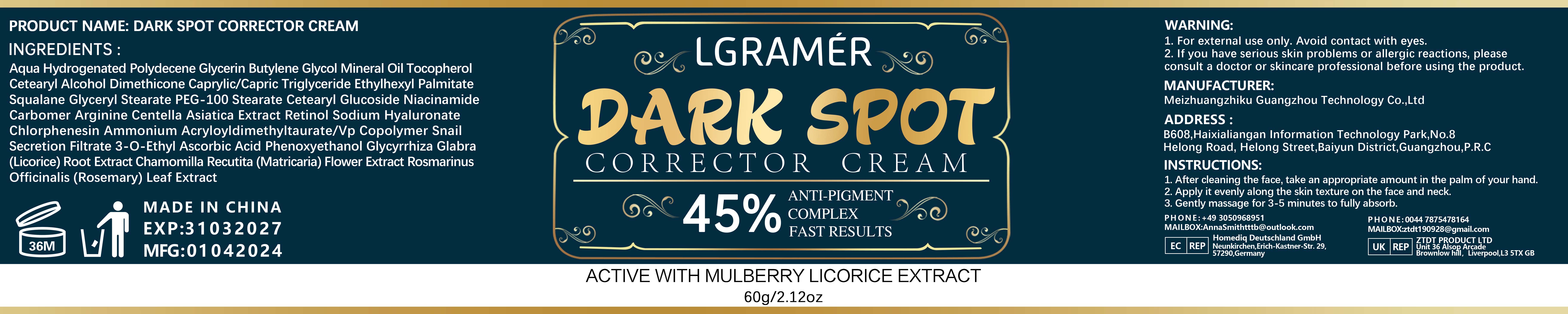 DRUG LABEL: LGRAMERCollagenmoisturizingcream
NDC: 84350-077 | Form: CREAM
Manufacturer: Shenzhen Sihal Juntong Technology Co. Ltd
Category: otc | Type: HUMAN OTC DRUG LABEL
Date: 20240905

ACTIVE INGREDIENTS: SQUALANE 1 g/60 mg
INACTIVE INGREDIENTS: WATER

ACTIVE INGREDIENT

1.5%YALURONIC ACID

INACTIVE INGREDIENT

Waler 5%水的5%

PURPOSE

Moisturizing 保湿

WARNING:
1. For external use only, Avoid contact with eyes.2. lf you have serious skin problems or allergic reactions, pleaseconsult a doctor or skincare professional before using the product.

DO NOT USE

lf you have allergic reactions, stop to use如有过敏反应，请停止使用

WHEN USING

1.After cleansing the body, take an appropriate amount of foot cream on the palm of your hand

2. Gently apply it evenly on the desired area
3. Massage gently until fuly absorbed.

Keep out of reach of children

INDICATIONS AND USAGE

INSTRUCTIONS:
1.After cleansing the body, take an appropriate amount of foot cream on the palm of your hand

2. Gently apply it evenly on the desired area
3. Massage gently until fully absorbed.

DOSAGE AND ADMINISTRATION

appropiate amount 适量

PACKAGE LABEL

60g NDC 84350-077-01